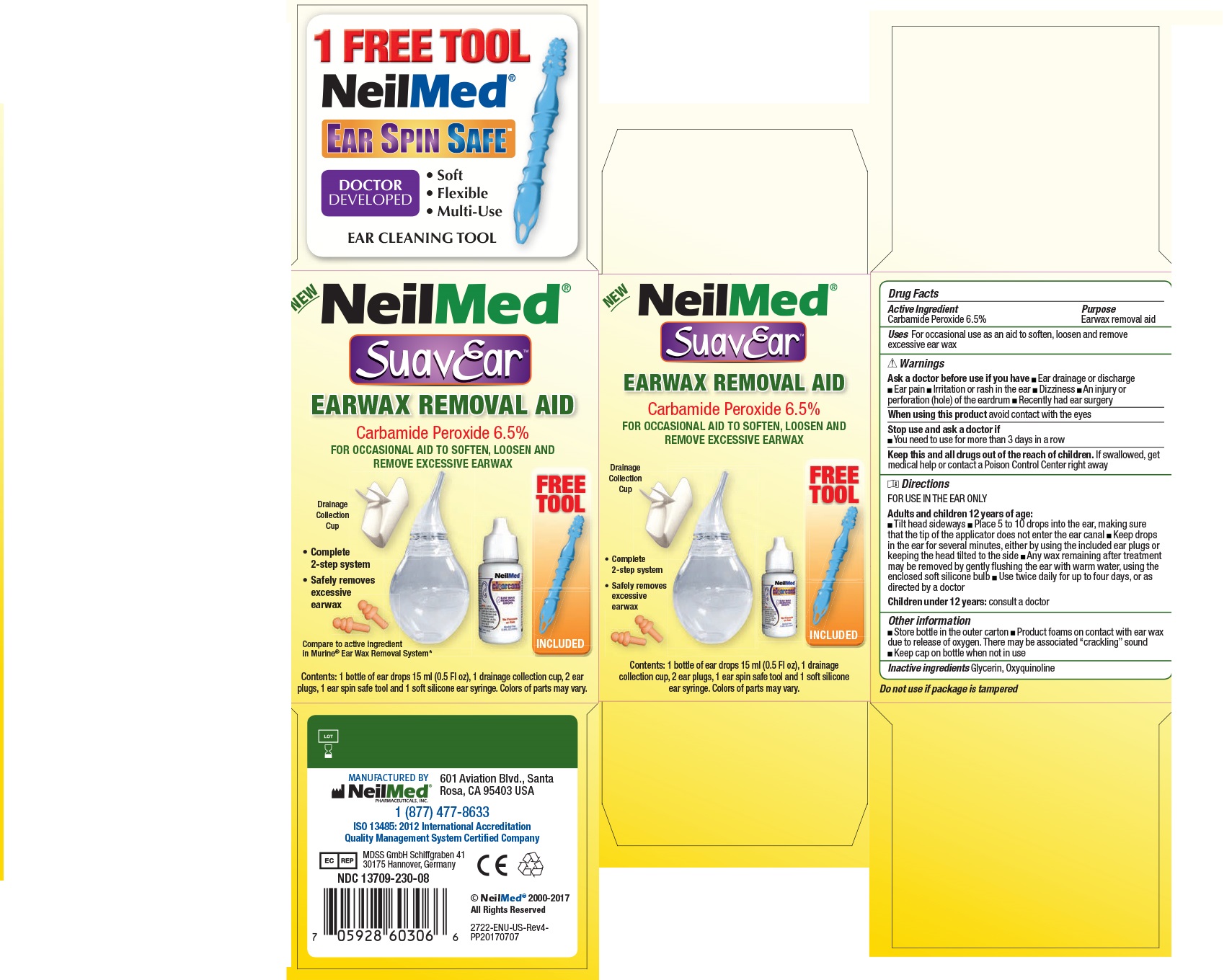 DRUG LABEL: SuavEar
NDC: 13709-233 | Form: SOLUTION/ DROPS
Manufacturer: NeilMed Pharmaceuticals Inc.
Category: otc | Type: HUMAN OTC DRUG LABEL
Date: 20160309

ACTIVE INGREDIENTS: CARBAMIDE PEROXIDE 65 mg/1 mL
INACTIVE INGREDIENTS: GLYCERIN; OXYQUINOLINE

SuavEar

Carbamide Peroxide 6.5%

DOSAGE AND ADMINISTRATION

For use in the ear only.

Tilt head sideways. Place 5 to 10 drops in the ear, making sure that the tip of the applicator does not enter the ear canal. Keep drops in the ear for several minutes, either by using the included ear plugs or keeping the head tilted to the side. Any wax remaining after treatment may be removed by gently flushing the ear with warm water, using the enclosed soft silicone bulb. Use twice daily for up to four days, or as directed by the doctor.

Warnings

Ask a doctor before use if

- you have ear drainage or discharge
- Ear pain
- Irritation or rash in the ear
- Dizziness
- An injury or perforation (hole) in the eardrum
- Recently had ear surgery

Whe using this product avoid contact with the eyes.

Stop use and ask a doctor if

- You need to use it for more than 3 days in a row.

List of inactive ingredients

Glycerin, Oxyquinoline

Ear canal cleaning

For occasional aid to soften, loosen and remove excessive earwax

Purpose

For occasional aid to soften, loosen and remove excessive earwax.

Keep out of reach of children.